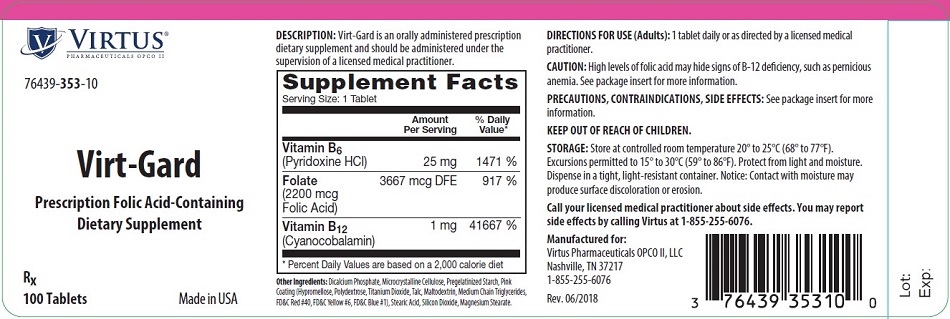 DRUG LABEL: Virt-Gard
NDC: 76439-353 | Form: TABLET
Manufacturer: Virtus Pharmaceuticals
Category: other | Type: DIETARY SUPPLEMENT
Date: 20191210

ACTIVE INGREDIENTS: PYRIDOXINE HYDROCHLORIDE 25 mg/1 1; FOLIC ACID 2.2 mg/1 1; CYANOCOBALAMIN 1 mg/1 1
INACTIVE INGREDIENTS: DIBASIC CALCIUM PHOSPHATE DIHYDRATE; MICROCRYSTALLINE CELLULOSE; STARCH, CORN; STEARIC ACID; SILICON DIOXIDE; MAGNESIUM STEARATE; HYPROMELLOSE, UNSPECIFIED; POLYDEXTROSE; TITANIUM DIOXIDE; TALC; MALTODEXTRIN; MEDIUM-CHAIN TRIGLYCERIDES; FD&C RED NO. 40; FD&C YELLOW NO. 6; FD&C BLUE NO. 1

Virt-Gard

HEALTH CLAIM

76439-353-10

Rx

Prescription Folic Acid-Containing
Dietary Supplement

DESCRIPTION

Virt-Gard is an orally administered prescription dietary supplement and should be administered under the supervision of a licensed medical practitioner.

Supplement Facts
Serving Size: 1 Tablet
 | Amount Per Serving | % Daily Value*
Vitamin B6
(Pyridoxine HCl) | 25 mg | 1471%
Folate; (2200 mcg Folic Acid) | 3667 mcg DFE | 917%
Vitamin B12
(Cyanocobalamin) | 1 mg | 41667%
*Percent Daily Values are based on a 2,000 calorie diet.

Other Ingredients: Dicalcium Phosphate, Microcrystalline Cellulose, Pregelatinized Starch, Pink Coating (Hypromellose, Polydextrose, Titanium Dioxide, Talc, Maltodextrin, Medium Chain Triglycerides, FD&C Red #40, FD&C Yellow #6, FD&C Blue #1), Stearic Acid, Silicon Dioxide, Magnesium Stearate.

INDICATIONS AND USAGE

Virt-Gard tablets are indicated for nutritional support and folic acid supplementation. This statement has not been evaluated by the Food and Drug Administration. This product is not intended to diagnose, treat, cure, or prevent any disease.

CONTRAINDICATIONS

This product is contraindicated in people with known history of hypersensitivity to any of the ingredients.

CAUTIONS

High levels of folic acid may, especially in older adults, hide signs of vitamin B-12 deficiency (such as pernicious anemia, a condition that can cause nerve damage).

Pediatric Use

Safety and effectiveness in pediatric patients have not been established.

SIDE EFFECTS

Allergic sensitization has been reported following oral administration of folic acid. Paresthesia, somnolence, nausea and headaches have been reported with pyridoxine hydrochloride.

Mild transient diarrhea, polycythemia vera, itching, transitory exanthema and the feeling of swelling of the entire body have been associated with cyanocobalamin.

DIRECTIONS FOR USE (Adults)

1 tablet daily or as directed by a licensed medical practitioner.

HOW SUPPLIED

Supplied as round, pink tablets imprinted with "V353," dispensed in bottles of 100 tablets.

76439-353-10

STORAGE

Store at controlled room temperature 20° to 25°C (68° to 77°F), excursions permitted to 15° to 30°C (59° to 86°F) Protect from light and moisture. Dispense in a tight, light-resistant container. Notice: Contact with moisture may produce surface discoloration or erosion.

Call your licensed medical practitioner about side effects. You may report side effects by calling Virtus at 1-855-255-6076.

KEEP OUT OF REACH OF CHILDREN.

Rx

Manufactured for:
Virtus Pharmaceuticals OPCO II, LLC
Nashville, TN 37217
1-855-255-6076

Made in USA

Rev. 06/2018

PRINCIPAL DISPLAY PANEL - 100 Tablet Bottle Label

VIRTUS®
PHARMACEUTICALS OPCO II

76439-353-10

Virt-Gard

Prescription Folic Acid-Containing
Dietary Supplement

Rx
100 Tablets
Made in USA